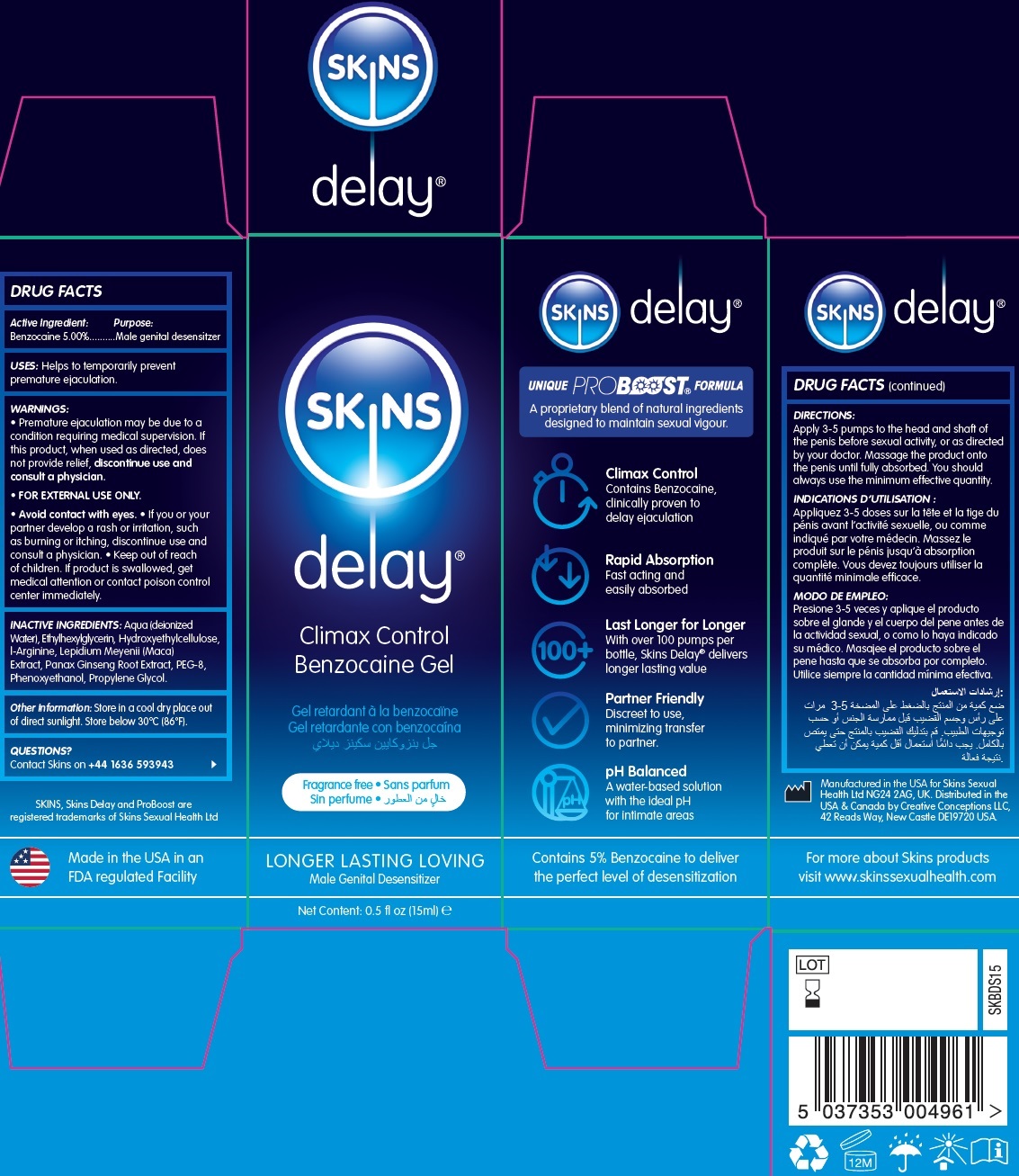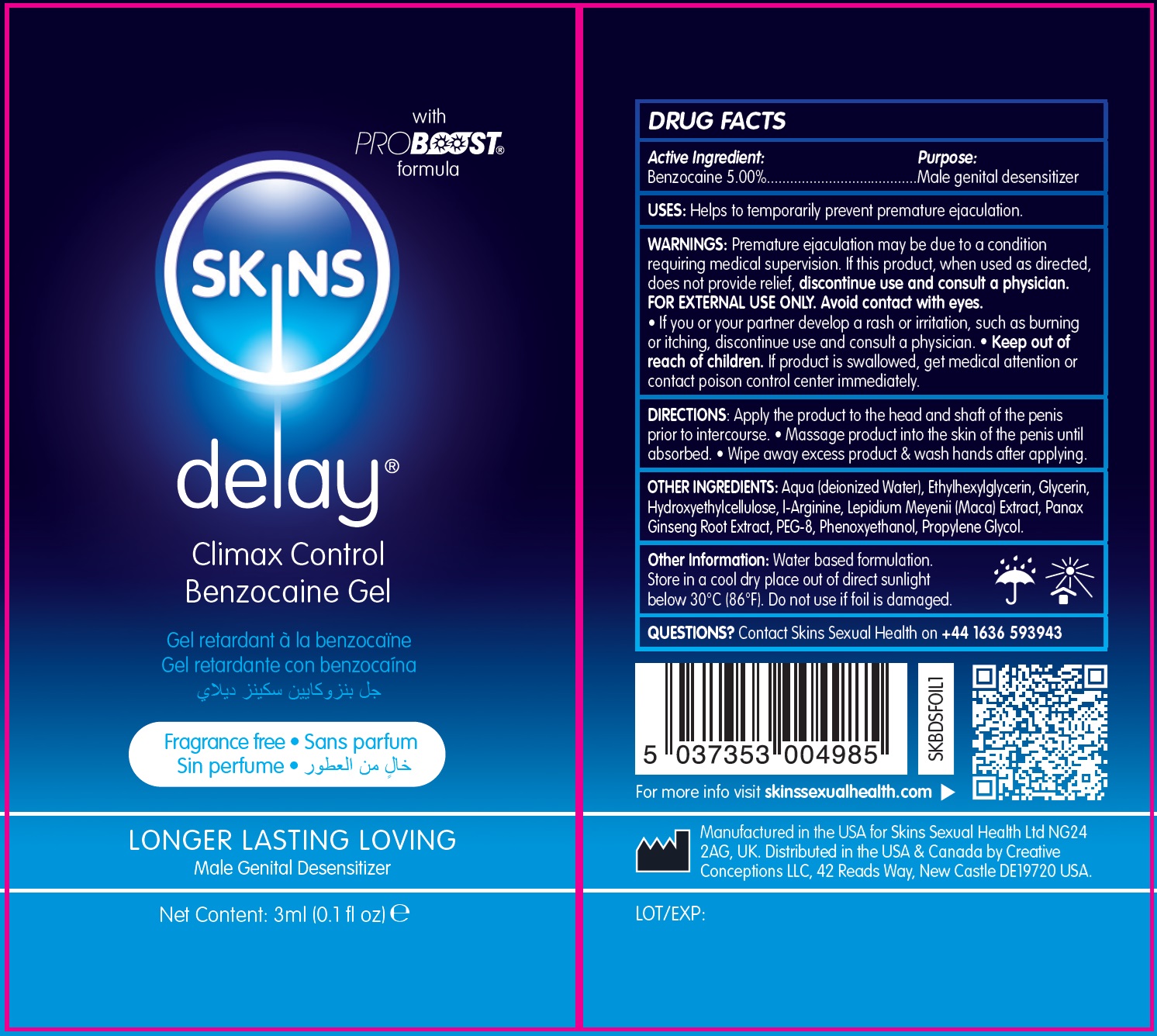 DRUG LABEL: SKINS DELAY Climax Control Benzocaine Gel
NDC: 81923-365 | Form: GEL
Manufacturer: SKINS SEXUAL HEALTH LIMITED
Category: otc | Type: HUMAN OTC DRUG LABEL
Date: 20240716

ACTIVE INGREDIENTS: BENZOCAINE 50 mg/1 mL
INACTIVE INGREDIENTS: ALOE VERA LEAF; ETHYLHEXYLGLYCERIN; HYDROXYETHYL CELLULOSE, UNSPECIFIED; ARGININE; ASIAN GINSENG; POLYETHYLENE GLYCOL 400; PHENOXYETHANOL; PROPYLENE GLYCOL

SKINS DELAY Climax Control Benzocaine Gel

Active Ingredient:

Benzocaine 5.00%

Purpose:

Male genital desensitizer

USES:

Helps to temporarily prevent premature ejaculation.

WARNINGS:

Premature ejaculation may be due to a condition requiring medical supervision. If this product, when used as directed, does not provide relief, discontinue use and consult a physician. • If you or your partner develop a rash or irritation, such as burning or itching, discontinue use and consult a physician.
FOR EXTERNAL USE ONLY. Avoid contact with eyes.

Keep out of reach of children.

• If product is swallowed, get medical attention or contact poison control center immediately.

DIRECTIONS:

Apply the product to the head and shaft of the penis prior to intercourse. • Massage product into the skin of the penis until it is absorbed. • Wipe away any excess product.

INACTIVE INGREDIENTS:

Aqua (deionized Water), Ethylhexylglycerin, Hydroxyethylcellulose, l-Arginine, Lepidium Meyenii (Maca) Extract, Panax Ginseng Root Extract, PEG-8, Phenoxyethanol, Propylene Glycol.

Other Information:

• Store in a cool dry place out of direct sunlight below 30°C (86°F). Do not use if foil is damaged.

QUESTIONS?

Contact Skins on +44 1636 593943